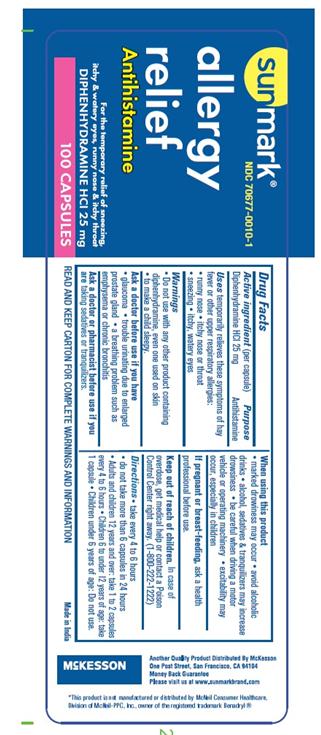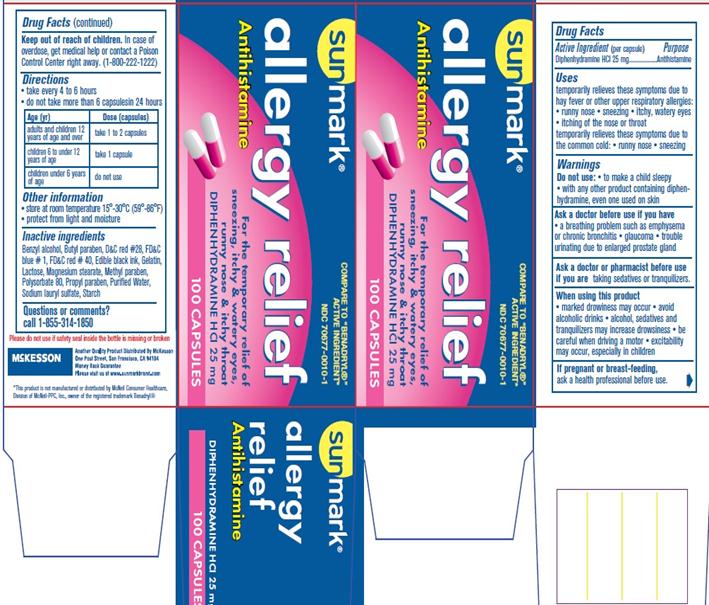 DRUG LABEL: Allergy
NDC: 70677-0010 | Form: CAPSULE
Manufacturer: Mckesson
Category: otc | Type: HUMAN OTC DRUG LABEL
Date: 20161217

ACTIVE INGREDIENTS: DIPHENHYDRAMINE HYDROCHLORIDE 25 mg/1 1
INACTIVE INGREDIENTS: BENZYL ALCOHOL; BUTYLPARABEN; D&C RED NO. 28; FD&C BLUE NO. 1; FD&C RED NO. 40; GELATIN; LACTOSE; MAGNESIUM STEARATE; METHYLPARABEN; PROPYLPARABEN; POLYSORBATE 80; SODIUM LAURYL SULFATE; STARCH, CORN

DIPHENHYDRAMINE HCl 25mg, USP

Active Ingredient

(per capsule)

Diphenhydramine HCl 25 mg

Purpose

Antihistamine

Uses

temporarily relieves these symptoms of hay fever or other upper respiratory allergies:

- runny nose
- itching of the nose or throat
- sneezing
- itchy, watery eyes
  temporarily relieves these symptoms due to the common cold:
- runny nose
- sneezing

Warnings

Do not use

- to make a child sleepy
- with any other product containing diphenhydramine, even one used on skin
  Ask a doctor before use if you have
- a breathing problem such as emphysema or chronic bronchitis
- glaucoma
- trouble urinating due to an enlarged prostate gland
  Ask a doctor or pharmacist before use if you are taking sedatives or tranquilizers
  When using this product
- you may get very drowsy
- avoid alcoholic drinks
- alcohol, sedatives & tranquilizers may increase drowsiness
- be careful when driving a motor vehicle or operating machinery
- excitability may occur, especially in children
  If pregnant or breast-feeding, ask a health professional before use.

Keep out of reach of children.

In case of overdose, get medical help or contact a Poison Control Center right away. (1-800-222-1222)

Directions

- take every 4 to 6 hours
- do not take more than 6 tablets in 24 hours
  Age (Yr) | Dose (capsules)
  Adults and children 12 years of age and over | Take 1 to 2 capsules
  Children 6 to under 12 years of age | Take 1 capsule
  Children under 6 years of age | do not use

Other Information

- store at room temperature between 15°-30°C (59°-86°F)
- protect from light and moisture

Inactive Ingredients

Benzyl alcohol, Butyl paraben, D&C red # 28, FD&C blue # 1, FD&C red # 40, Edible black ink, gelatin, lactose, Magnesium stearate, Methyl paraben, polysorbate 80, Propyl paraben, Purified water, Sodium lauryl sulfate, Starch

Questions or Comments

Call 1-855-314-1850

PACKAGE LABEL.PRINCIPAL DISPLAY PANEL

NDC 70677-0010-1